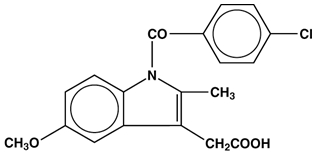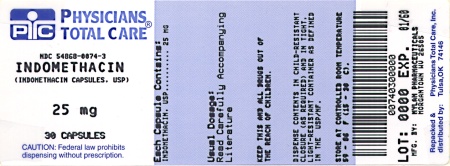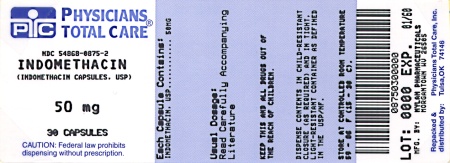 DRUG LABEL: Indomethacin
NDC: 54868-0074 | Form: CAPSULE
Manufacturer: Physicians Total Care, Inc.
Category: prescription | Type: HUMAN PRESCRIPTION DRUG LABEL
Date: 20080313

ACTIVE INGREDIENTS: INDOMETHACIN 25 mg/1 1
INACTIVE INGREDIENTS: SILICON DIOXIDE; GELATIN; FD&C GREEN NO. 3; MAGNESIUM STEARATE; CELLULOSE, MICROCRYSTALLINE; POWDERED CELLULOSE; SODIUM LAURYL SULFATE; SODIUM STARCH GLYCOLATE TYPE A POTATO; TITANIUM DIOXIDE; D&C YELLOW NO. 10; FERROSOFERRIC OXIDE; FD&C BLUE NO. 1; FD&C BLUE NO. 2; FD&C RED NO. 40; PROPYLENE GLYCOL

BOXED WARNING

Cardiovascular Risk

- • NSAIDs may cause an increased risk of serious cardiovascular thrombotic events, myocardial infarction, and stroke, which can be fatal. This risk may increase with duration of use. Patients with cardiovascular disease or risk factors for cardiovascular disease may be at greater risk (see WARNINGS).
- Indomethacin is contraindicated for the treatment of perioperative pain in the setting of coronary artery bypass graft (CABG) surgery (see WARNINGS).

Gastrointestinal Risk

- NSAIDs cause an increased risk of serious gastrointestinal adverse events including bleeding, ulceration, and perforation of the stomach or intestines, which can be fatal. These events can occur at any time during use and without warning symptoms. Elderly patients are at greater risk for serious gastrointestinal events (see WARNINGS).

DESCRIPTION

Indomethacin Capsules, USP for oral administration are provided in two dosage strengths which contain either 25 mg or 50 mg of indomethacin. Indomethacin is a non-steroidal anti-inflammatory indole derivative designated chemically as 1-(4-chlorobenzoyl)-5-methoxy-2-methyl-1H-indole-3-acetic acid.

The structural formula is:

C19H16CINO4 M.W. 357.79

Indomethacin, USP is practically insoluble in water and sparingly soluble in alcohol. It has a pKa of 4.5 and is stable in neutral or slightly acidic media and decomposes in strong alkali.

Each capsule for oral administration contains 25 mg or 50 mg of indomethacin and the following inactive ingredients: colloidal silicon dioxide, gelatin, FD&C Green No. 3, magnesium stearate, microcrystalline cellulose, powdered cellulose, sodium lauryl sulfate, sodium starch glycolate, titanium dioxide and D&C Yellow No. 10.

The imprinting ink contains the following: black iron oxide, D&C Yellow No. 10 Aluminum Lake, FD&C Blue No. 1 Aluminum Lake, FD&C Blue No. 2 Aluminum Lake, FD&C Red No. 40 Aluminum Lake, pharmaceutical glaze and propylene glycol.

CLINICAL PHARMACOLOGY

Indomethacin is a non-steroidal anti-inflammatory drug (NSAID) that exhibits antipyretic and analgesic properties. Its mode of action, like that of other anti-inflammatory drugs, is not known. However, its therapeutic action is not due to pituitary-adrenal stimulation.

Indomethacin is a potent inhibitor of prostaglandin synthesis in vitro. Concentrations are reached during therapy which have been demonstrated to have an effect in vivo as well. Prostaglandins sensitize afferent nerves and potentiate the action of bradykinin in inducing pain in animal models. Moreover, prostaglandins are known to be among the mediators of inflammation. Since indomethacin is an inhibitor of prostaglandin synthesis, its mode of action may be due to a decrease of prostaglandins in peripheral tissues.

Indomethacin has been shown to be an effective anti-inflammatory agent, appropriate for long-term use in rheumatoid arthritis, ankylosing spondylitis, and osteoarthritis.

Indomethacin affords relief of symptoms; it does not alter the progressive course of the underlying disease.

Indomethacin suppresses inflammation in rheumatoid arthritis as demonstrated by relief of pain, and reduction of fever, swelling and tenderness. Improvement in patients treated with indomethacin for rheumatoid arthritis has been demonstrated by a reduction in joint swelling, average number of joints involved, and morning stiffness; by increased mobility as demonstrated by a decrease in walking time; and by improved functional capability as demonstrated by an increase in grip strength. Indomethacin may enable the reduction of steroid dosage in patients receiving steroids for the more severe forms of rheumatoid arthritis. In such instances the steroid dosage should be reduced slowly and the patients followed very closely for any possible adverse effects.

Indomethacin has been reported to diminish basal and CO2 stimulated cerebral blood flow in healthy volunteers following acute oral and intravenous administration. In one study, after one week of treatment with orally administered indomethacin, this effect on basal cerebral blood flow had disappeared. The clinical significance of this effect has not been established.

Indomethacin capsules have been found effective in relieving the pain, reducing the fever, swelling, redness, and tenderness of acute gouty arthritis (see INDICATIONS AND USAGE).

Following single oral doses of indomethacin capsules 25 mg or 50 mg, indomethacin is readily absorbed, attaining peak plasma concentrations of about 1 and 2 mcg/mL, respectively, at about 2 hours. Orally administered indomethacin capsules are virtually 100% bioavailable, with 90% of the dose absorbed within 4 hours. A single 50 mg dose of indomethacin oral suspension was found to be bioequivalent to a 50 mg indomethacin capsule when each was administered with food.

Indomethacin is eliminated via renal excretion, metabolism, and biliary excretion. Indomethacin undergoes appreciable enterohepatic circulation. The mean half-life of indomethacin is estimated to be about 4.5 hours. With a typical therapeutic regimen of 25 mg or 50 mg t.i.d., the steady-state plasma concentrations of indomethacin are an average 1.4 times those following the first dose.

Indomethacin exists in the plasma as the parent drug and its desmethyl, desbenzoyl, and desmethyl-desbenzoyl metabolites, all in the unconjugated form. About 60% of an oral dosage is recovered in urine as drug and metabolites (26% as indomethacin and its glucuronide), and 33% is recovered in feces (1.5% as indomethacin).

About 99% of indomethacin is bound to protein in plasma over the expected range of therapeutic plasma concentrations. Indomethacin has been found to cross the blood-brain barrier and the placenta.

INDICATIONS AND USAGE

Carefully consider the potential benefits and risks of indomethacin capsules and other treatment options before deciding to use indomethacin. Use the lowest effective dose for the shortest duration consistent with individual patient treatment goals (see WARNINGS).

Indomethacin has been found effective in active stages of the following:

1. Moderate to severe rheumatoid arthritis including acute flares of chronic disease.
2. Moderate to severe ankylosing spondylitis.
3. Moderate to severe osteoarthritis.
4. Acute painful shoulder (bursitis and/or tendinitis).
5. Acute gouty arthritis.

CONTRAINDICATIONS

Indomethacin is contraindicated in patients with known hypersensitivity to indomethacin or the excipients (see DESCRIPTION).

Indomethacin should not be given to patients who have experienced asthma, urticaria, or allergic-type reactions after taking aspirin or other NSAIDs. Severe, rarely fatal, anaphylactic/anaphylactoid reactions to NSAIDs have been reported in such patients (see WARNINGS: Anaphylactic/Anaphylactoid Reactions, and PRECAUTIONS: General: Preexisting Asthma).

Indomethacin is contraindicated for the treatment of perioperative pain in the setting of coronary artery bypass graft (CABG) surgery (see WARNINGS).

WARNINGS

Cardiovascular Effects

Cardiovascular Thrombotic Events

Clinical trials of several COX-2 selective and nonselective NSAIDs of up to 3 years duration have shown an increased risk of serious cardiovascular (CV) thrombotic events, myocardial infarction, and stroke, which can be fatal. All NSAIDs, both COX-2 selective and nonselective, may have a similar risk. Patients with known CV disease or risk factors for CV disease may be at greater risk. To minimize the potential risk for an adverse CV event in patients treated with an NSAID, the lowest effective dose should be used for the shortest duration possible. Physicians and patients should remain alert for the development of such events, even in the absence of previous CV symptoms. Patients should be informed about the signs and/or symptoms of serious CV events and the steps to take if they occur.

There is no consistent evidence that concurrent use of aspirin mitigates the increased risk of serious CV thrombotic events associated with NSAID use. The concurrent use of aspirin and an NSAID does increase the risk of serious GI events (see WARNINGS: Gastrointestinal Effects).

Two large, controlled, clinical trials of a COX-2 selective NSAID for the treatment of pain in the first 10 to 14 days following CABG surgery found an increased incidence of myocardial infarction and stroke (see CONTRAINDICATIONS).

Hypertension

NSAIDs, including indomethacin, can lead to onset of new hypertension or worsening of preexisting hypertension, either of which may contribute to the increased incidence of CV events. Patients taking thiazides or loop diuretics may have impaired response to these therapies when taking NSAIDs. NSAIDs, including indomethacin, should be used with caution in patients with hypertension. Blood pressure (BP) should be monitored closely during the initiation of NSAID treatment and throughout the course of therapy.

Congestive Heart Failure and Edema

Fluid retention and edema have been observed in some patients taking NSAIDs. Indomethacin should be used with caution in patients with fluid retention or heart failure.

In a study of patients with severe heart failure and hyponatremia, indomethacin was associated with significant deterioration of circulatory hemodynamics, presumably due to inhibition of prostaglandin dependent compensatory mechanisms.

Gastrointestinal Effects

Risk of Ulceration, Bleeding, and Perforation

NSAIDs, including indomethacin, can cause serious gastrointestinal (GI) adverse events including inflammation, bleeding, ulceration, and perforation of the esophagus, stomach, small intestine, or large intestine, which can be fatal. These serious adverse events can occur at any time, with or without warning symptoms, in patients treated with NSAIDs. Only one in five patients, who develop a serious upper GI adverse event on NSAID therapy is symptomatic. Upper GI ulcers, gross bleeding, or perforation caused by NSAIDs occur in approximately 1% of patients treated for 3 to 6 months, and in about 2 to 4% of patients treated for one year. These trends continue with longer duration of use, increasing the likelihood of developing a serious GI event at some time during the course of therapy. However, even short-term therapy is not without risk.

Rarely, in patients taking indomethacin, intestinal ulceration has been associated with stenosis and obstruction. Gastrointestinal bleeding without obvious ulcer formation and perforation of preexisting sigmoid lesions (diverticulum, carcinoma, etc.) have occurred. Increased abdominal pain in ulcerative colitis patients or the development of ulcerative colitis and regional ileitis have been reported to occur rarely.

NSAIDs should be prescribed with extreme caution in those with a prior history of ulcer disease or gastrointestinal bleeding. Patients with a prior history of peptic ulcer disease and/or gastrointestinal bleeding who use NSAIDs have a greater than 10-fold increased risk for developing a GI bleed compared to patients with neither of these risk factors. Other factors that increase the risk for GI bleeding in patients treated with NSAIDs include concomitant use of oral corticosteroids or anticoagulants, longer duration of NSAID therapy, smoking, use of alcohol, older age, and poor general health status. Most spontaneous reports of fatal GI events are in elderly or debilitated patients and therefore, special care should be taken in treating this population.

To minimize the potential risk for an adverse GI event in patients treated with an NSAID, the lowest effective dose should be used for the shortest possible duration. Patients and physicians should remain alert for signs and symptoms of GI ulceration and bleeding during NSAID therapy and promptly initiate additional evaluation and treatment if a serious GI adverse event is suspected. This should include discontinuation of the NSAID until a serious GI adverse event is ruled out. For high risk patients, alternate therapies that do not involve NSAIDs should be considered.

Renal Effects

Long-term administration of NSAIDs has resulted in renal papillary necrosis and other renal injury. Renal toxicity has also been seen in patients in whom renal prostaglandins have a compensatory role in the maintenance of renal perfusion. In these patients, administration of a non-steroidal anti-inflammatory drug may cause a dose dependent reduction in prostaglandin formation and, secondarily, in renal blood flow, which may precipitate over renal decompensation. Patients at greatest risk of this reaction are those with impaired renal function, heart failure, liver dysfunction, those taking diuretics and ACE inhibitors, patients with volume depletion, and the elderly. Discontinuation of NSAID therapy is usually followed by recovery to the pretreatment state.

Increases in serum potassium concentration, including hyperkalemia, have been reported with use of indomethacin, even in some patients without renal impairment. In patients with normal renal function, these effects have been attributed to a hyporeninemic-hypoaldosteronism state (see PRECAUTIONS: Drug Interactions).

Advanced Renal Disease

No information is available from controlled clinical studies regarding the use of indomethacin in patients with advanced renal disease. Therefore, treatment with indomethacin is not recommended in these patients with advanced renal disease. If indomethacin therapy must be initiated, close monitoring of the patient’s renal function is advisable.

Anaphylactic/Anaphylactoid Reactions

As with other NSAIDs, anaphylactic/anaphylactoid reactions may occur in patients without known prior exposure to indomethacin. Indomethacin should not be given to patients with the aspirin triad. This symptom complex typically occurs in asthmatic patients who experience rhinitis with or without nasal polyps, or who exhibit severe, potentially fatal bronchospasm after taking aspirin or other NSAIDs (see CONTRAINDICATIONS and PRECAUTIONS: General: Preexisting Asthma). Emergency help should be sought in cases where an anaphylactic/anaphylactoid reaction occurs.

Skin Reactions

NSAIDs, including indomethacin, can cause serious skin adverse events such as exfoliative dermatitis, Stevens-Johnson Syndrome (SJS), and toxic epidermal necrolysis (TEN), which can be fatal. These serious events may occur without warning. Patients should be informed about the signs and symptoms of serious skin manifestations and use of the drug should be discontinued at the first appearance of skin rash or any other sign of hypersensitivity.

Pregnancy

In late pregnancy, as with other NSAIDs, indomethacin should be avoided because it may cause premature closure of the ductus arteriosus.

Ocular Effects

Corneal deposits and retinal disturbances, including those of the macula, have been observed in some patients who had received prolonged therapy with indomethacin. The prescribing physician should be alert to the possible association between the changes noted and indomethacin. It is advisable to discontinue therapy if such changes are observed. Blurred vision may be a significant symptom and warrants a thorough ophthalmological examination. Since these changes may be asymptomatic, ophthalmologic examination at periodic intervals is desirable in patients where therapy is prolonged.

Central Nervous System Effects

Indomethacin may aggravate depression or other psychiatric disturbances, epilepsy, and parkinsonism, and should be used with considerable caution in patients with these conditions. If severe CNS adverse reactions develop, indomethacin should be discontinued.

Indomethacin may cause drowsiness; therefore, patients should be cautioned about engaging in activities requiring mental alertness and motor coordination, such as driving a car. Indomethacin may also cause headache. Headache which persists despite dosage reduction requires cessation of therapy with indomethacin.

PRECAUTIONS

General

Indomethacin cannot be expected to substitute for corticosteroids or to treat corticosteroid insufficiency. Abrupt discontinuation of corticosteroids may lead to disease exacerbation. Patients on prolonged corticosteroid therapy should have their therapy tapered slowly if a decision is made to discontinue corticosteroids.

The pharmacological activity of indomethacin in reducing fever and inflammation may diminish the utility of these diagnostic signs in detecting complications of presumed noninfectious, painful conditions.

Hepatic Effects

Borderline elevations of one or more liver tests may occur in up to 15% of patients taking NSAIDs, including indomethacin. These laboratory abnormalities may progress, may remain unchanged, or may be transient with continuing therapy. Notable elevations of ALT or AST (approximately three or more times the upper limit of normal) have been reported in approximately 1% of patients in clinical trials with NSAIDs. In addition, rare cases of severe hepatic reactions, including jaundice and fatal fulminant hepatitis, liver necrosis and hepatic failure, some of them with fatal outcomes have been reported.

A patient with symptoms and/or signs suggesting liver dysfunction, or in whom an abnormal liver test values has occured, should be evaluated for evidence of the development of a more severe hepatic reaction while on therapy with indomethacin. If clinical signs and symptoms consistent with liver disease develop, or if systemic manifestations occur (e.g., eosinophilia, rash, etc.), indomethacin should be discontinued.

Hematological Effects

Anemia is sometimes seen in patients receiving NSAIDs, including indomethacin. This may be due to fluid retention, occult or gross GI blood loss, or an incompletely described effect upon erythropoiesis. Patients on long-term treatment with NSAIDs, including indomethacin, should have their hemoglobin or hematocrit checked if they exhibit any signs or symptoms of anemia.

NSAIDs inhibit platelet aggregation and have been shown to prolong bleeding time in some patients. Unlike aspirin, their effect on platelet function is quantitatively less, of shorter duration, and reversible. Patients receiving indomethacin who may be adversely affected by alterations in platelet function, such as those with coagulation disorders or patients receiving anticoagulants, should be carefully monitored.

Preexisting Asthma

Patients with asthma may have aspirin-sensitive asthma. The use of aspirin in patients with aspirin-sensitive asthma has been associated with severe bronchospasm which can be fatal. Since cross-reactivity, including bronchospasm, between aspirin and other non-steroidal anti-inflammatory drugs has been reported in such aspirin-sensitive patients, indomethacin should not be administered to patients with this form of aspirin sensitivity and should be used with caution in patients with preexisting asthma.

Information for Patients

Patients should be informed of the following information before initiating therapy with an NSAID and periodically during the course of ongoing therapy. Patients should also be encouraged to read the NSAID Medication Guide that accompanies each prescription dispensed.

1. Indomethacin, like other NSAIDs, may cause serious CV side effects, such as MI or stroke, which may result in hospitalization and even death. Although serious CV events can occur without warning symptoms, patients should be alert for the signs and symptoms of chest pain, shortness of breath, weakness, slurring of speech, and should ask for medical advice when observing any indicative sign or symptoms. Patients should be apprised of the importance of this follow-up (see WARNINGS: Cardiovascular Effects).
2. Indomethacin, like other NSAIDs, can cause GI discomfort and, rarely, serious GI side effects, such as ulcers and bleeding, which may result in hospitalization and even death. Although serious GI tract ulcerations and bleeding can occur without warning symptoms, patients should be alert for the signs and symptoms of ulcerations and bleeding, and should ask for medical advice when observing any indicative signs or symptoms including epigastric pain, dyspepsia, melena, and hematemesis. Patients should be apprised of the importance of this follow-up (see WARNINGS: Gastrointestinal Effects: Risk of Ulceration, Bleeding, and Perforation).
3. Indomethacin, like other NSAIDs, can cause serious skin side effects such as exfoliative dermatitis, SJS, and TEN, which may result in hospitalizations and even death. Although serious skin reactions may occur without warning, patients should be alert for the signs and symptoms of skin rash and blisters, fever, or other signs of hypersensitivity such as itching, and should ask for medical advice when observing any indicative signs or symptoms. Patients should be advised to stop the drug immediately if they develop any type of rash and contact their physicians as soon as possible.
4. Patients should promptly report signs or symptoms of unexplained weight gain or edema to their physicians.
5. Patients should be informed of the warning signs and symptoms of hepatotoxicity (e.g., nausea, fatigue, lethargy, pruritus, jaundice, right upper quadrant tenderness and “flu-like” symptoms). If these occur, patients should be instructed to stop therapy and seek immediate medical therapy.
6. Patients should be informed of the signs of an anaphylactic/anaphylactoid reaction (e.g. difficulty breathing, swelling of the face or throat). If these occur, patients should be instructed to seek immediate emergency help (see WARNINGS).
7. In late pregnancy, as with other NSAIDs, indomethacin should be avoided because it may cause premature closure of the ductus arteriosus.

Laboratory Tests

Because serious GI tract ulcerations and bleeding can occur without warning symptoms, physicians should monitor for signs or symptoms of GI bleeding. Patients on long-term treatment with NSAIDs should have their CBC and a chemistry profile checked periodically. If clinical signs and symptoms consistent with liver or renal disease develop, systemic manifestations occur (e.g., eosinophilia, rash, etc.) or if abnormal liver tests persist or worsen, indomethacin should be discontinued.

Drug Interactions

ACE Inhibitors and Angiotensin II Antagonists

Reports suggest that NSAIDs may diminish the antihypertensive effect of ACE inhibitors and angiotensin II antagonists. Indomethacin can reduce the antihypertensive effects of captopril and losartan. These interactions should be given consideration in patients taking NSAIDs concomitantly with ACE inhibitors or angiotensin II antagonists. In some patients with compromised renal function, the coadministration of an NSAID and an ACE inhibitor or an angiotensin II antagonist may result in further deterioration of renal function, including possible acute renal failure, which is usually reversible.

Aspirin

When indomethacin is administered with aspirin, its protein binding is reduced, although the clearance of free indomethacin is not altered. The clinical significance of this interaction is not known.

The use of indomethacin in conjunction with aspirin or other salicylates is not recommended. Controlled clinical studies have shown that the combined use of indomethacin and aspirin does not produce any greater therapeutic effect than the use of indomethacin alone. In a clinical study of the combined use of indomethacin and aspirin, the incidence of gastrointestinal side effects was significantly increased with combined therapy.

In a study in normal volunteers, it was found that chronic concurrent administration of 3.6 g of aspirin per day decreases indomethacin blood levels approximately 20%.

Beta-Adrenoceptor Blocking Agents

Blunting of the antihypertensive effect of beta-adrenoceptor blocking agents by non-steroidal anti-inflammatory drugs including indomethacin has been reported. Therefore, when using these blocking agents to treat hypertension, patients should be observed carefully in order to confirm that the desired therapeutic effect has been obtained.

Cyclosporin

Administration of non-steroidal anti-inflammatory drugs concomitantly with cyclosporine has been associated with an increase in cyclosporine-induced toxicity, possibly due to decreased synthesis of renal prostacyclin. NSAIDs should be used with caution in patients taking cyclosporine, and renal function should be carefully monitored.

Diflunisal

In normal volunteers receiving indomethacin, the administration of diflunisal decreased the renal clearance and significantly increased the plasma levels of indomethacin. In some patients, combined use of indomethacin and diflunisal has been associated with fatal gastrointestinal hemorrhage. Therefore, diflunisal and indomethacin should not be used concomitantly.

Digoxin

Indomethacin given concomitantly with digoxin has been reported to increase the serum concentration and prolong the half-life of digoxin. Therefore, when indomethacin and digoxin are used concomitantly, serum digoxin levels should be closely monitored.

Diuretics

In some patients, the administration of indomethacin can reduce the diuretic, natriuretic, and antihypertensive effects of loop, potassium-sparing, and thiazide diuretics. This response has been attributed to inhibition of renal prostaglandin synthesis.

Indomethacin reduces basal plasma renin activity (PRA), as well as those elevations of PRA induced by furosemide administration, or salt or volume depletion. These facts should be considered when evaluating plasma renin activity in hypertensive patients.

It has been reported that the addition of triamterene to a maintenance schedule of indomethacin resulted in reversible acute renal failure in two of four healthy volunteers. Indomethacin and triamterene should not be administered together.

Indomethacin and potassium-sparing diuretics each may be associated with increased serum potassium levels. The potential effects of indomethacin and potassium-sparing diuretics on potassium kinetics and renal function should be considered when these agents are administered concurrently. Most of the above effects concerning diuretics have been attributed, at least in part, to mechanisms involving inhibition of prostaglandin synthesis by indomethacin.

During concomitant therapy with NSAIDs, the patient should be observed closely for signs of renal failure (see WARNINGS: Renal Effects), as well as to assure diuretic efficacy.

Lithium

Indomethacin capsules 50 mg t.i.d. produced a clinically relevant elevation of plasma lithium and reduction in renal lithium clearance in psychiatric patients and normal subjects with steady-state plasma lithium concentrations. This effect has been attributed to inhibition of prostaglandin synthesis. As a consequence, when NSAIDs and lithium are given concomitantly, the patient should be carefully observed for signs of lithium toxicity. (Read circulars for lithium preparations before use of such concomitant therapy.) In addition, the frequency of monitoring serum lithium concentration should be increased at the outset of such combination drug treatment.

Methotrexate

NSAIDs have been reported to competitively inhibit methotrexate accumulation in rabbit kidney slices. This may indicate that they could enhance the toxicity of methotrexate. Caution should be used when NSAIDs are administered concomitantly with methotrexate.

NSAIDs

The concomitant use of indomethacin with other NSAIDs is not recommended due to the increased possibility of gastrointestinal toxicity, with little or no increase in efficacy.

Oral anticoagulants

Clinical studies have shown that indomethacin does not influence the hypoprothrombinemia produced by anticoagulants. However, when any additional drug, including indomethacin, is added to the treatment of patients on anticoagulant therapy, the patients should be observed for alterations of the prothrombin time. In post-marketing experience, bleeding has been reported in patients on concomitant treatment with anticoagulants and indomethacin. Caution should be exercised when indomethacin and anticoagulants are administered concomitantly. The effects of warfarin and NSAIDs on GI bleeding are synergistic, such that users of both drugs together have a risk of serious GI bleeding higher than users of either drug alone.

Probenecid

When indomethacin is given to patients receiving probenecid, the plasma levels of indomethacin are likely to be increased. Therefore, a lower total daily dosage of indomethacin may produce a satisfactory therapeutic effect. When increases in the dose of indomethacin are made, they should be made carefully and in small increments.

Drug/Laboratory Test Interactions

False-negative results in the dexamethasone suppression test (DST) in patients being treated with indomethacin have been reported. Thus, results of the DST should be interpreted with caution in these patients.

Carcinogenesis, Mutagenesis, Impairment of Fertility

In an 81-week chronic oral toxicity study in the rat at doses up to 1 mg/kg/day, indomethacin had no tumorigenic effect.

Indomethacin produced no neoplastic or hyperplastic changes related to treatment in carcinogenic studies in the rat (dosing period 73 to 110 weeks) and the mouse (dosing period 62 to 88 weeks) at doses up to 1.5 mg/kg/day.

Indomethacin did not have any mutagenic effect in in vitro bacterial tests (Ames test and E. coli with or without metabolic activation) and a series of in vivo tests including the host-mediated assay, sex-linked recessive lethals in Drosophila, and the micronucleus test in mice.

Indomethacin at dosage levels up to 0.5 mg/kg/day had no effect on fertility in mice in a two generation reproduction study or a two litter reproduction study in rats.

Pregnancy

Teratogenic Effects. Pregnancy Category C

Teratogenic studies were conducted in mice and rats at dosages of 0.5, 1.0, 2.0, and 4.0 mg/kg/day. Except for retarded fetal ossification at 4 mg/kg/day considered secondary to the decreased average fetal weights, no increase in fetal malformations was observed as compared with control groups. Other studies in mice reported in the literature using higher doses (5 to 15 mg/kg/day) have described maternal toxicity and death, increased fetal resorptions, and fetal malformations. Comparable studies in rodents using high doses of aspirin have shown similar maternal and fetal effects. However, animal reproduction studies are not always predictive of human response. There are no adequate and well controlled studies in pregnant women.

Indomethacin should be used during pregnancy only if the potential benefit justifies the potential risk to the fetus.

Nonteratogenic Effects

Because of the known effects of non-steroidal anti-inflammatory drugs on the fetal cardiovascular system (closure of ductus arteriosus), use during pregnancy (particularly late pregnancy) should be avoided.

The known effects of indomethacin and other drugs of this class on the human fetus during the third trimester of pregnancy include: constriction of the ductus arteriosus prenatally, tricuspid incompetence, and pulmonary hypertension; nonclosure of the ductus arteriosus postnatally which may be resistant to medical management; myocardial degenerative changes, platelet dysfunction with resultant bleeding, intracranial bleeding, renal dysfunction or failure, renal injury/dysgenesis which may result in prolonged or permanent renal failure, oligohydramnios, gastrointestinal bleeding or perforation, and increased risk of necrotizing enterocolitis.

In rats and mice, 4.0 mg/kg/day given during the last 3 days of gestation caused a decrease in maternal weight gain and some maternal and fetal deaths. An increased incidence of neuronal necrosis in the diencephalon in the live born fetuses was observed. At 2.0 mg/kg/day, no increase in neuronal necrosis was observed as compared to the control groups. Administration of 0.5 or 4.0 mg/kg/day during the first 3 days of life did not cause an increase in neuronal necrosis at either dose level.

Labor and Delivery

In rat studies with NSAIDs, as with other drugs known to inhibit prostaglandin synthesis, an increased incidence of dystocia, delayed parturition, and decreased pup survival occurred. The effects of indomethacin on labor and delivery in pregnant women are unknown.

Nursing Mothers

Indomethacin is excreted in the milk of lactating mothers. Indomethacin is not recommended for use in nursing mothers.

Pediatric Use

Safety and effectiveness in pediatric patients 14 years of age and younger have not been established.

Indomethacin should not be prescribed for pediatric patients 14 years of age and younger unless toxicity or lack of efficacy associated with other drugs warrants the risk.

In experience with more than 900 pediatric patients reported in the literature or to the manufacturer who were treated with Capsules indomethacin, side effects in pediatric patients were comparable to those reported in adults. Experience in pediatric patients has been confined to the use of Capsules indomethacin.

If a decision is made to use indomethacin for pediatric patients 2 years of age or older, such patients should be monitored closely and periodic assessment of liver function is recommended. There have been cases of hepatotoxicity reported in pediatric patients with juvenile rheumatoid arthritis, including fatalities. If indomethacin treatment is instituted, a suggested starting dose is 1 to 2 mg/kg/day given in divided doses. Maximum daily dosage should not exceed 3 mg/kg/day or 150 to 200 mg/day, whichever is less. Limited data are available to support the use of a maximum daily dosage of 4mg/kg/day or 150 to 200 mg/day, whichever is less. As symptoms subside, the total daily dosage should be reduced to the lowest level required to control symptoms, or the drug should be discontinued.

Geriatric Use

As with any NSAID, caution should be exercised in treating the elderly (65 years and older) since advancing age appears to increase the possibility of adverse reactions (see WARNINGS, Gastrointestinal Effects: Risk of Ulceration, Bleeding, and Perforation and DOSAGE AND ADMINISTRATION). Elderly patients seem to tolerate ulceration or bleeding less well than other individuals and many spontaneous reports of fatal GI events are in this population (see WARNINGS: Gastrointestinal Effects: Risk of Ulceration, Bleeding, and Perforation).

Indomethacin may cause confusion or, rarely, psychosis (see ADVERSE REACTIONS); physicians should remain alert to the possibility of such adverse effects in the elderly.

This drug is known to be substantially excreted by the kidney and the risk of toxic reactions to this drug may be greater in patients with impaired renal function. Because elderly patients are more likely to have decreased renal function, care should be taken in dose selection and it may be useful to monitor renal function (see WARNINGS: Renal Effects).

ADVERSE REACTIONS

The adverse reactions for indomethacin capsules listed in the following table have been arranged into two groups: (1) incidence greater than 1%; and (2) incidence less than 1%. The incidence for group (1) was obtained from 33 double-blind controlled clinical trials reported in the literature (1,092 patients). The incidence for group (2) was based on reports in clinical trials, in the literature, and on voluntary reports since marketing. The probability of a causal relationship exists between indomethacin and these adverse reactions, some of which have been reported only rarely.

Incidence greater than 1%

GASTROINTESTINAL
nausea* with or without vomiting
dyspepsia* (including indigestion, heartburn and epigastric pain)
diarrhea
abdominal distress or pain
constipation

CENTRAL NERVOUS SYSTEM
headache (11.7%)
dizziness*
vertigo
somnolence
depression and fatigue (including malaise and listlessness)

SPECIAL SENSES
tinnitus

CARDIOVASCULAR
none

METABOLIC
none

INTEGUMENTARY
none

HEMATOLOGIC
none

HYPERSENSITIVITY
none

GENITOURINARY
none

MISCELLANEOUS
none

* Reactions occurring in 3% to 9% of patients treated with indomethacin. (Those reactions occurring in less than 3% of the patients are unmarked.)

Incidence less than 1%

GASTROINTESTINAL
anorexia
bloating (includes distention)
flatulence
peptic ulcer
gastroenteritis
rectal bleeding
proctitis
single or multiple ulcerations, including perforation and hemorrhage of the esophagus, stomach, duodenum or small and large intestines
intestinal ulceration associated with stenosis and obstruction
gastrointestinal bleeding without obvious ulcer formation and perforation of preexisting sigmoid lesions (diverticulum, carcinoma, etc.) development of ulcerative colitis and regional ileitis
ulcerative stomatitis
toxic hepatitis and jaundice (some fatal cases have been reported)
intestinal strictures (diaphragms)

CENTRAL NERVOUS SYSTEM
anxiety (includes nervousness)
muscle weakness
involuntary muscle movements
insomnia
muzziness
psychic disturbances including psychotic episodes
mental confusion
drowsiness
light-headedness
syncope
paresthesia
aggravation of epilepsy and parkinsonism
depersonalization
coma
peripheral neuropathy
convulsions
dysarthria

SPECIAL SENSES
ocular-corneal deposits and retinal disturbances, including those of the macula, have been reported in some patients on prolonged therapy with indomethacin
blurred vision
diplopia
hearing disturbances, deafness

CARDIOVASCULAR
congestive heart failure
hypertension
hypotension
tachycardia
chest pain
arrhythmia; palpitations

METABOLIC
edema
weight gain
fluid retention
flushing or sweating
hyperglycemia
glycosuria
hyperkalemia

INTEGUMENTARY
pruritus
rash; urticaria
petechiae or ecchymosis
exfoliative dermatitis
erythema nodosum
loss of hair
Stevens-Johnson Syndrome
erythema multiforme
toxic epidermal necrolysis

HEMATOLOGIC
leukopenia
bone marrow depression
anemia secondary to obvious or occult gastrointestinal bleeding
aplastic anemia
hemolytic anemia
agranulocytosis
thrombocytopenic purpura
disseminated intravascular coagulation

HYPERSENSITIVITY
acute anaphylaxis
acute respiratory distress
rapid fall in blood pressure resembling a shock-like state
angioedema
dyspnea
asthma
purpura
angiitis
pulmonary edema
fever

GENITOURINARY
hematuria
vaginal bleeding
proteinuria, nephrotic syndrome, interstitial nephritis
BUN elevation
renal insufficiency, including renal failure

MISCELLANEOUS
epistaxis
breast changes, including enlargement and tenderness, or gynecomastia

Causal Relationship Unknown

Other reactions have been reported but occurred under circumstances where a causal relationship could not be established. However, in these rarely reported events, the possibility cannot be excluded. Therefore, these observations are being listed to serve as alerting information to physicians:

Cardiovascular: thrombophlebitis

Hematologic: Although there have been several reports of leukemia, the supporting information is weak.

Genitourinary: urinary frequency

A rare occurrence of fulminant necrotizing fasciitis, particularly in association with Group A β-hemolytic streptococcus, has been described in persons treated with non-steroidal anti-inflammatory agents, including indomethacin, sometimes with fatal outcome (see also PRECAUTIONS: General).

OVERDOSAGE

The following symptoms may be observed following overdosage: nausea, vomiting, intense headache, dizziness, mental confusion, disorientation, or lethargy. There have been reports of paresthesias, numbness and convulsions.

Treatment is symptomatic and supportive. The stomach should be emptied as quickly as possible if the ingestion is recent. If vomiting has not occurred spontaneously, the patient should be induced to vomit with syrup of ipecac. If the patient is unable to vomit, gastric lavage should be performed. Once the stomach has been emptied, 25 g or 50 g of activated charcoal may be given. Depending on the condition of the patient, close medical observation and nursing care may be required. The patient should be followed for several days because gastrointestinal ulceration and hemorrhage have been reported as adverse reactions of indomethacin. Use of antacids may be helpful.

The oral LD50 of indomethacin in mice and rats (based on 14 day mortality response) was 50 and 12 mg/kg, respectively.

DOSAGE AND ADMINISTRATION

Carefully consider the potential benefits and risks of indomethacin and other treatment options before deciding to use indomethacin. Use the lowest effective dose for the shortest duration consistent with individual patient treatment goals (see WARNINGS).

After observing the response to initial therapy with indomethacin, the dose and frequency should be adjusted to suit an individual patient’s needs.

Indomethacin is available as 25 mg and 50 mg capsules.

Adverse reactions appear to correlate with the size of the dose of indomethacin in most patients but not all. Therefore, every effort should be made to determine the smallest effective dosage for the individual patient.

Pediatric Use

Indomethacin ordinarily should not be prescribed for pediatric patients 14 years of age and under (see WARNINGS).

Adult Use

Dosage Recommendations for Active Stages of the Following:

1. Moderate to severe rheumatoid arthritis including acute flares of chronic disease; moderate to severe ankylosing spondylitis; and moderate to severe osteoarthritis.

Suggested Dosage: Indomethacin capsules 25 mg b.i.d. or t.i.d. If this is well tolerated, increase the daily dosage by 25 mg or by 50 mg, if required by continuing symptoms, at weekly intervals until a satisfactory response is obtained or until a total daily dose of 150 mg to 200 mg is reached. DOSES ABOVE THIS AMOUNT GENERALLY DO NOT INCREASE THE EFFECTIVENESS OF THE DRUG.

In patients who have persistent night pain and/or morning stiffness, the giving of a large portion, up to a maximum of 100 mg, of the total daily dose at bedtime may be helpful in affording relief. The total daily dose should not exceed 200 mg. In acute flares of chronic rheumatoid arthritis, it may be necessary to increase the dosage by 25 mg or, if required, by 50 mg daily.

If minor adverse effects develop as the dosage is increased, reduce the dosage rapidly to a tolerated dose and OBSERVE THE PATIENT CLOSELY.

If severe adverse reactions occur, STOP THE DRUG. After the acute phase of the disease is under control, an attempt to reduce the daily dose should be made repeatedly until the patient is receiving the smallest effective dose or the drug is discontinued.

Careful instructions to, and observations of, the individual patient are essential to the prevention of serious, irreversible, including fatal, adverse reactions.

As advancing years appear to increase the possibility of adverse reactions, indomethacin should be used with greater care in the elderly (see PRECAUTIONS: Geriatric Use).

2. Acute painful shoulder (bursitis and/or tendinitis).

Initial Dose: 75 mg to 150 mg daily in 3 or 4 divided doses. The drug should be discontinued after the signs and symptoms of inflammation have been controlled for several days. The usual course of therapy is 7 to 14 days.

3. Acute gouty arthritis.

Suggested Dosage: Indomethacin capsules 50 mg t.i.d. until pain is tolerable. The dose should then be rapidly reduced to complete cessation of the drug. Definite relief of pain has been reported within 2 to 4 hours. Tenderness and heat usually subside in 24 to 36 hours, and swelling gradually disappears in 3 to 5 days.

HOW SUPPLIED

Indomethacin Capsules, USP are available containing either 25 mg or 50 mg of Indomethacin, USP.

The 25 mg capsule is a hard-shell gelatin capsule with a light green opaque cap and a light green opaque body axially printed with MYLAN over 143 in black ink on both the cap and body. The capsule is filled with a white powder blend. They are available as follows:

Bottles of 15 | NDC 54868-0074-8
Bottles of 20 | NDC 54868-0074-9
Bottles of 30 | NDC 54868-0074-3
Bottles of 40 | NDC 54868-0074-4
Bottles of 60 | NDC 54868-0074-5
Bottles of 90 | NDC 54868-0074-7
Bottles of 100 | NDC 54868-0074-2

The 50 mg capsule is a hard-shell gelatin capsule with a light green opaque cap and a light green opaque body axially printed with MYLAN over 147 in black ink on both the cap and body. The capsule is filled with a white powder blend. They are available as follows:

Bottles of 15 | NDC 54868-0875-7
Bottles of 20 | NDC 54868-0875-6
Bottles of 30 | NDC 54868-0875-2
Bottles of 40 | NDC 54868-0875-4
Bottles of 60 | NDC 54868-0875-0
Bottles of 90 | NDC 54868-0875-5
Bottles of 100 | NDC 54868-0875-1

Store at 20° to 25°C (68° to 77°F). [See USP for Controlled Room Temperature.]

Protect from light.

Dispense in a tight, light-resistant container as defined in the USP using a child-resistant closure.

PHARMACIST: Dispense a Medication Guide with each prescription.

Mylan Pharmaceuticals Inc.
Morgantown, WV 26505

REVISED MARCH 2008
INDO:R26mc

Relabeling and Repackaging by:
Physicians Total Care, Inc.
Tulsa, OK 74146

Medication Guide for
Non-Steroidal Anti-Inflammatory Drugs
(NSAIDs)

(See the end of this Medication Guide for a list of prescription NSAID medicines.)

What is the most important information I should know about medicines called Non-Steroidal Anti-Inflammatory Drugs (NSAIDs)?

NSAID medicines may increase the chance of a heart attack or stroke that can lead to death. This chance increases:
  - with longer use of NSAID medicines
  - in people who have heart disease
NSAID medicines should never be used right before or after a heart surgery called a “coronary artery bypass graft (CABG).”
NSAID medicines can cause ulcers and bleeding in the stomach and intestines at any time during treatment. Ulcers and bleeding:
  - can happen without warning symptoms
  - may cause death
The chance of a person getting an ulcer or bleeding increases with:
  - taking medicines called “corticosteroids” and “anticoagulants”
  - longer use
  - smoking
  - drinking alcohol
  - older age
  - having poor health
NSAID medicines should only be used:
  - exactly as prescribed
  - at the lowest dose possible for your treatment
  - for the shortest time needed

What are Non-Steroidal Anti-Inflammatory Drugs (NSAIDs)?

NSAID medicines are used to treat pain and redness, swelling, and heat (inflammation) from medical conditions such as:

- different types of arthritis
- menstrual cramps and other types of short-term pain

Who should not take a Non-Steroidal Anti-Inflammatory Drug (NSAID)?

Do not take an NSAID medicine:

- if you had an asthma attack, hives, or other allergic reaction with aspirin or any other NSAID medicine
- for pain right before or after heart bypass surgery

Tell your healthcare provider:

- about all of your medical conditions.
- about all of the medicines you take. NSAIDs and some other medicines can interact with each other and cause serious side effects. Keep a list of your medicines to show to your healthcare provider and pharmacist.
- if you are pregnant. NSAID medicines should not be used by pregnant women late in their pregnancy.
- if you are breastfeeding. Talk to your doctor.

What are the possible side effects of Non-Steroidal Anti-Inflammatory Drugs (NSAIDs)?

Serious side effects include:

• heart attack

• stroke

• high blood pressure

• heart failure from body swelling (fluid retention)

• kidney problems including kidney failure

• bleeding and ulcers in the stomach and intestine

• low red blood cells (anemia)

• life-threatening skin reactions

• life-threatening allergic reactions

• liver problems including liver failure

• asthma attacks in people who have asthma

Other side effects include:

• stomach pain

• constipation

• diarrhea

• gas

• heartburn

• nausea

• vomiting

• dizziness

Get emergency help right away if you have any of the following symptoms:

- shortness of breath or trouble breathing
- chest pain
- weakness in one part or side of your body
- slurred speech
- swelling of the face or throat

Stop your NSAID medicine and call your healthcare provider right away if you have any of the following symptoms:

- nausea
- more tired or weaker than usual
- itching
- your skin or eyes look yellow
- stomach pain
- flu-like symptoms
- vomit blood
- there is blood in your bowel movement or it is black and sticky like tar
- unusual weight gain
- skin rash or blisters with fever
- swelling of the arms and legs, hands and feet

These are not all the side effects with NSAID medicines. Talk to your healthcare provider or pharmacist for more information about NSAID medicines.

Other information about Non-Steroidal Anti-Inflammatory Drugs (NSAIDs)

- Aspirin is an NSAID medicine but it does not increase the chance of a heart attack. Aspirin can cause bleeding in the brain, stomach, and intestines. Aspirin can also cause ulcers in the stomach and intestines.
- Some of these NSAID medicines are sold in lower doses without a prescription (over-the-counter). Talk to your healthcare provider before using over-the-counter NSAIDs for more than 10 days.

NSAID medicines that need a prescription
Generic Name | Tradename
Celecoxib | Celebrex
Diclofenac | Cataflam, Voltaren, Arthrotec (combined with misoprostol)
Diflunisal | Dolobid
Etodolac | Lodine, Lodine XL
Fenoprofen | Nalfon, Nalfon 200
Flurbiprofen | Ansaid
Ibuprofen | Motrin, Tab-Profen, Vicoprofen (combined with hydrocodone), Combunox (combined with oxycodone)
Indomethacin | Indocin, Indocin SR, Indo-Lemmon, Indomethagan
Ketoprofen | Oruvail
Ketorolac | Toradol
Mefenamic Acid | Ponstel
Meloxicam | Mobic
Nabumetone | Relafen
Naproxen | Naprosyn, Anaprox, Anaprox DS, EC-Naproxyn, Naprelan, Naprapac (copackaged with lansoprazole)
Oxaprozin | Daypro
Piroxicam | Feldene
Sulindac | Clinoril
Tolmetin | Tolectin, Tolectin DS, Tolectin 600

Call your doctor for medical advice about side effects. You may report side effects to FDA at 1-800-FDA-1088.

This Medication Guide has been approved by the U.S. Food and Drug Administration.

PACKAGE LABEL

PRINCIPAL DISPLAY PANEL - 25 mg

ATTENTION:
Dispense with
Medication Guide

INDOMETHACIN
CAPSULES, USP
25 mg

(Rx only)

Each capsule contains:
Indomethacin, USP 25 mg

Dispense in a tight, light-resistant
container as defined in the USP
using a child-resistant closure.

Keep container tightly closed.

Keep this and all medication
out of the reach of children.

Store at 20° to 25°C (68° to 77°F).
[See USP for Controlled Room
Temperature.]

Protect from light.

Usual Adult Dosage: One or two
capsules 2 or 3 times a day. See
package outsert for full prescribing
information.

PACKAGE LABEL

PRINCIPAL DISPLAY PANEL - 50 mg

ATTENTION:
Dispense with
Medication Guide

INDOMETHACIN
CAPSULES, USP
50 mg

(Rx only)

Each capsule contains:
Indomethacin, USP 50 mg

Dispense in a tight, light-resistant
container as defined in the USP
using a child-resistant closure.

Keep container tightly closed.

Keep this and all medication
out of the reach of children.

Store at 20° to 25°C (68° to 77°F).
[See USP for Controlled Room
Temperature.]

Protect from light.

Usual Adult Dosage: One capsule
2 or 3 times a day. See package out-
sert for full prescribing
information.